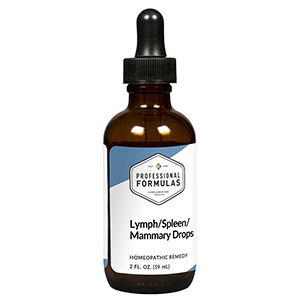 DRUG LABEL: Lymph/Spleen/Mammary Drops
NDC: 63083-5014 | Form: LIQUID
Manufacturer: Professional Complementary Health Formulas
Category: homeopathic | Type: HUMAN OTC DRUG LABEL
Date: 20190815

ACTIVE INGREDIENTS: ECHINACEA ANGUSTIFOLIA WHOLE 2 [hp_X]/59 mL; ARSENIC TRIOXIDE 6 [hp_X]/59 mL; CALCIUM SULFIDE 6 [hp_X]/59 mL; SUPEROXIDES 6 [hp_X]/59 mL; BOS TAURUS LYMPH VESSEL 6 [hp_X]/59 mL; SUS SCROFA MAMMARY GLAND 6 [hp_X]/59 mL; BOS TAURUS SPLEEN 6 [hp_X]/59 mL
INACTIVE INGREDIENTS: ALCOHOL; WATER

HLSM

ACTIVE INGREDIENTS

Echinacea angustifolia 2X
Arsenicum album 6X
Hepar sulphuris calcareum 6X
Superoxide dismutase (SOD) 6X
Lymph 6X, 12X, 30X, 60X, 100X
Mammary 6X, 12X, 30X, 60X, 100X
Spleen 6X, 12X, 30X, 60X, 100X

QUESTIONS

Professional Formulas

PO Box 2034 Lake Oswego, OR 97035

INDICATIONS

For the temporary relief of breast inflammation, tenderness, or pain, dry or itchy skin, mild abdominal discomfort, shortness of breath, weakness, or fatigue.*

PURPOSE

*Claims based on traditional homeopathic practice, not accepted medical evidence. Not FDA evaluated.

WARNINGS

Consult a doctor if condition worsens or if symptoms persist. Keep out of the reach of children. In case of overdose, get medical help or contact a poison control center right away. If pregnant or breastfeeding, ask a healthcare professional before use.

Keep out of the reach of children.

PREGNANCY OR BREAST FEEDING

If pregnant or breastfeeding, ask a healthcare professional before use.

DIRECTIONS

Place drops under tongue 30 minutes before/after meals. Adults and children 12 years and over: Take 10 drops up to 3 times per day. Consult a physician for use in children under 12 years of age.

OTHER INFORMATION

Tamper resistant. If seal is broken, do not use. After opening, close container tightly and store at room temperature away from heat.

INACTIVE INGREDIENTS

20% ethanol, purified water.

LABEL

Est 1985

Professional Formulas

Complementary Health

Lymph/Spleen/Mammary Drops

Homeopathic Remedy

2 FL. OZ. (59 mL)